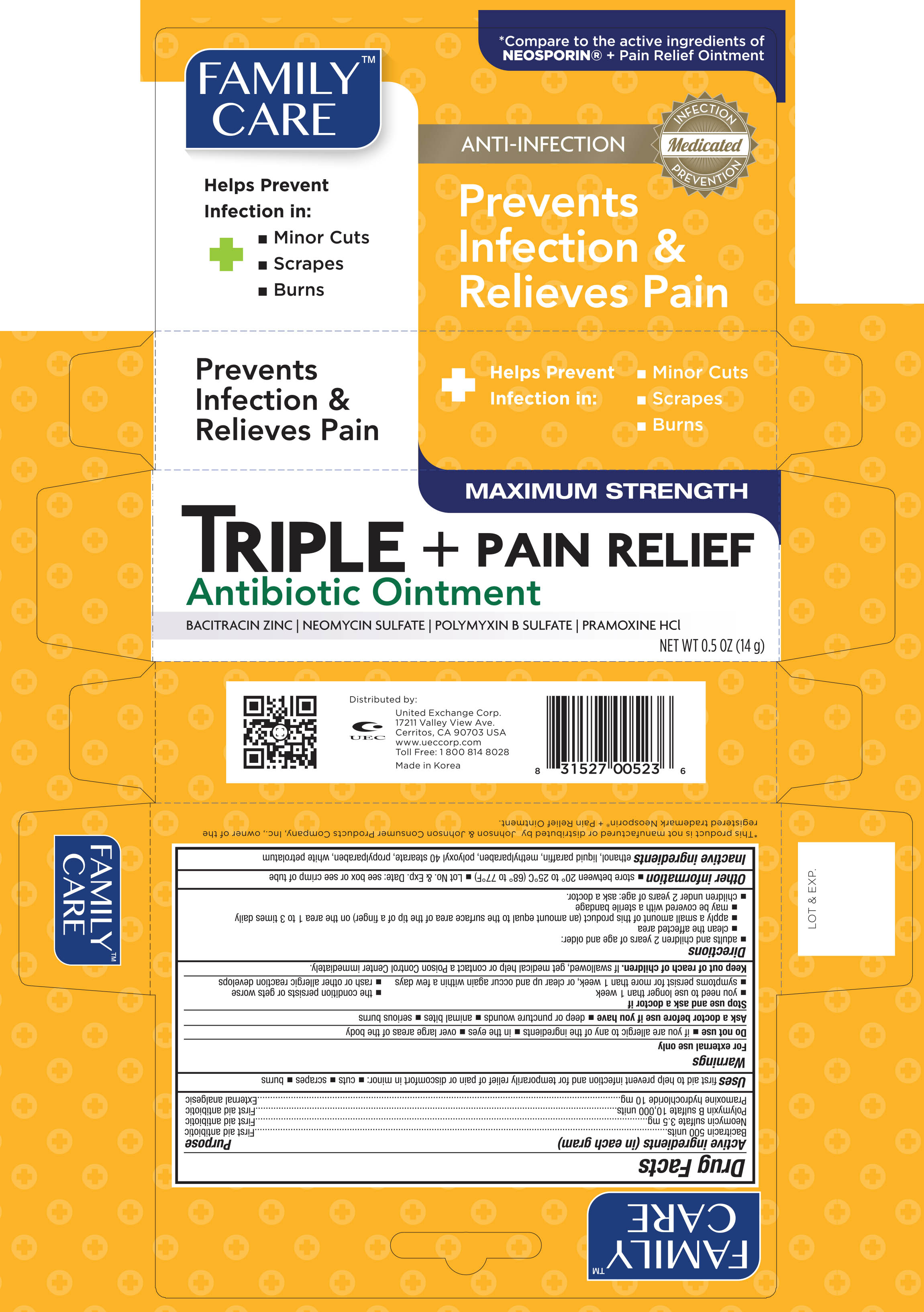 DRUG LABEL: Family Care Triple Antibiotic Plus Pain Relief
NDC: 65923-523 | Form: OINTMENT
Manufacturer: United Exchange Corp.
Category: otc | Type: HUMAN OTC DRUG LABEL
Date: 20160915

ACTIVE INGREDIENTS: POLYMYXIN B SULFATE 10000 [USP'U]/1 g; BACITRACIN 500 [USP'U]/1 g; NEOMYCIN SULFATE 3.5 mg/1 g; PRAMOXINE HYDROCHLORIDE 10 mg/1 g
INACTIVE INGREDIENTS: ALCOHOL; PARAFFIN; METHYLPARABEN; POLYOXYL 40 STEARATE; PROPYLPARABEN; PETROLATUM

Active ingredients (in each gram) Purpose

Bacitracin 500 units....................................................................... First aid antibiotic

Neomycin sulfate 3.5 mg................................................................ First aid antibiotic

Polymyxin B sulfate 10,000 units...................................................... First aid antibiotic

Pramoxine hydrochloride 10mg........................................................ First aid antibiotic

Uses

first aid to help prevent infection and for temporarily relief of pain or discomfort in minor:

- cuts
- scrapes
- burns

Warnings

For external use only

Do not use

- if you are allergic to any of the ingredients
- in the eyes
- over large areas of the body

Ask a doctor before use if you have

- deep or puncture wounds
- animal bites
- serious burns

Stop use and ask a doctor if

- you need to use longer than 1 week
- symptoms persist for more than 1 week, or clear up and occur again within a few days
- the condition persists or gets worse
- rash or allerfic reaction develops

Keep out of reach of children

If swallowed, get medical help or contact Poison Control Center immediately

Directions

- adults and children 2 years of age and older:
- clean the affected area
- apply a small amount of this product (an amount equal to the surface area of the tip of a finger) on the area 1 to 3 times daily
- may be covered with a stearile bandage
- children under 2 years of age: ask a doctor

Other information

- store between 20° to 25°C (68° to 77°F)
- Lot No. & Exp. Date: see box or see crimp of tube

Inactive ingredients

ethanol, liquid paraffin, methylparaben, polyoxyl 40 stearate, propylparaben, white petrolatum

DOSAGE AND ADMINISTRATION

Distributed by:

United Exchange Corp.

17211 Valley View Ave.

Cerritos CA, 90703 USA

Made in Korea